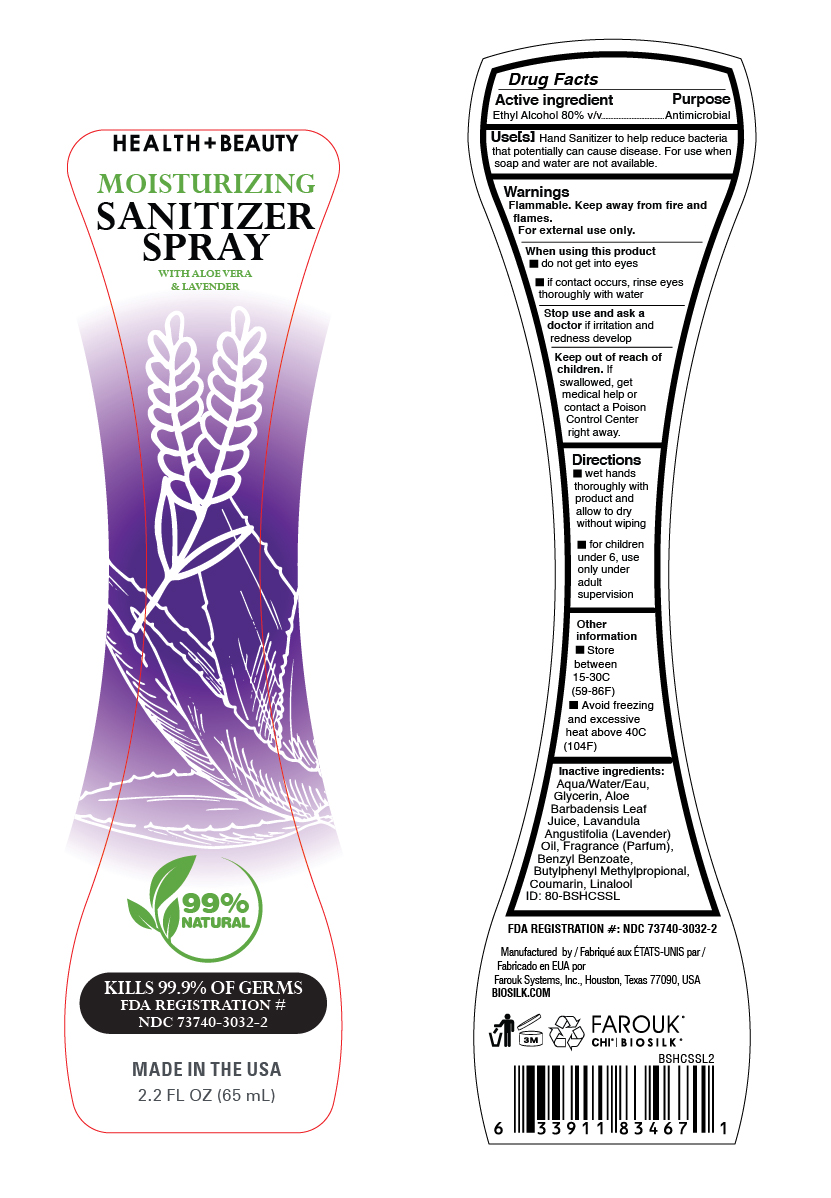 DRUG LABEL: Biosilk Lavender
NDC: 73740-3032 | Form: SPRAY
Manufacturer: Farouk Systems, Inc.
Category: otc | Type: HUMAN OTC DRUG LABEL
Date: 20201125

ACTIVE INGREDIENTS: ALCOHOL 80 g/100 g
INACTIVE INGREDIENTS: BENZYL BENZOATE 0.125 g/100 g; Glycerin 2 g/100 g; BUTYLPHENYL METHYLPROPIONAL 0.01875 g/100 g; COUMARIN 0.01 g/100 g; LINALOOL, (+/-)- 0.0075 g/100 g; WATER 22.749 g/100 g; ALOE VERA LEAF 0.001 g/100 g; FRAGRANCE LAVENDER ORC1800979 0.08875 g/100 g

Biosilk Health and Beauty Sanitizer Spray Lavender

Stop use and ask a doctor

Stop use and ask a
doctor if irritation and
redness develop

Active ingredient

Active ingredient Purpose
Ethyl Alcohol 80% v/v Antimicrobial

Stop use and ask a doctor

Stop use and ask a
doctor if irritation and
redness develop

Stop use and ask a doctor

Stop use and ask a
doctor if irritation and
redness develop

Keep out of reach of children.

Keep out of reach of
children. If
swallowed, get
medical help or
contact a Poison
Control Center
right away.

Use[s]

Use[s] Hand Sanitizer to help reduce bacteria
that potentially can cause disease. For use when
soap and water are not available.

Directions

wet hands
thoroughly with
product and
allow to dry
without wiping
for children
under 6, use
only under
adult
supervision

Inactive ingredients:

Aqua/Water/Eau
Glycerin
Aloe Barbadensis Leaf Juice
Fragrance (Parfum)
Benzyl Benzoate
Butylphenyl Methylpropional
Coumarin
Linalool

Warnings

Flammable. Keep away from fire and
flames.
For external use only.
When using this product
do not get into eyes
if contact occurs, rinse eyes
thoroughly with water
Stop use and ask a
doctor if irritation and
redness develop
Keep out of reach of
children. If
swallowed, get
medical help or
contact a Poison
Control Center
right away.

Use[s]

Use[s] Hand Sanitizer to help reduce bacteria
that potentially can cause disease. For use when
soap and water are not available.

Biosilk Health And Beauty Moisturizing Sanitizer Spray With Aloe Vera And Lavender

99% Natural

KILLS 99.9% OF GERMS

FDA REGISTRATION #

NDC 73740-3032-2

MADE IN THE USA

2.2 FL OZ (65 mL)